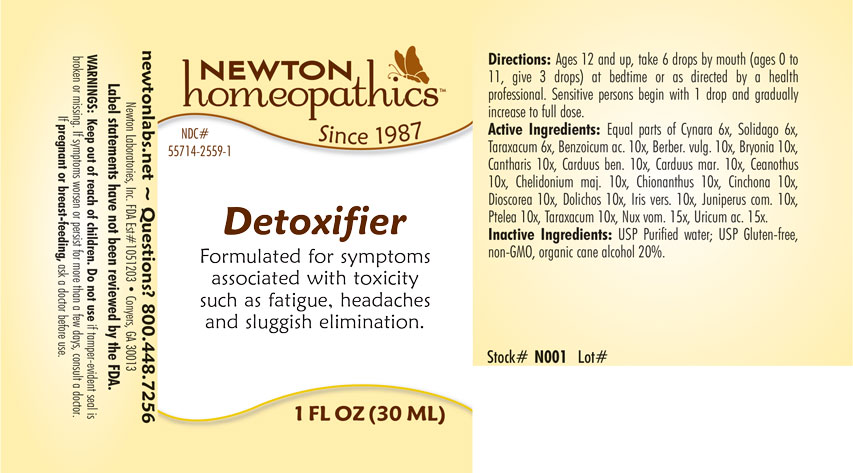 DRUG LABEL: Detoxifier
NDC: 55714-2559 | Form: LIQUID
Manufacturer: Newton Laboratories, Inc.
Category: homeopathic | Type: HUMAN OTC DRUG LABEL
Date: 20240307

ACTIVE INGREDIENTS: URIC ACID 15 [hp_X]/1 mL; BENZOIC ACID 10 [hp_X]/1 mL; BERBERIS VULGARIS ROOT BARK 10 [hp_X]/1 mL; BRYONIA ALBA ROOT 10 [hp_X]/1 mL; LYTTA VESICATORIA 10 [hp_X]/1 mL; CENTAUREA BENEDICTA 10 [hp_X]/1 mL; CEANOTHUS AMERICANUS LEAF 10 [hp_X]/1 mL; CHELIDONIUM MAJUS 10 [hp_X]/1 mL; CHIONANTHUS VIRGINICUS BARK 10 [hp_X]/1 mL; CINCHONA OFFICINALIS BARK 10 [hp_X]/1 mL; DIOSCOREA VILLOSA TUBER 10 [hp_X]/1 mL; MUCUNA PRURIENS FRUIT TRICHOME 10 [hp_X]/1 mL; IRIS VERSICOLOR ROOT 10 [hp_X]/1 mL; JUNIPER BERRY 10 [hp_X]/1 mL; STRYCHNOS NUX-VOMICA SEED 15 [hp_X]/1 mL; PTELEA TRIFOLIATA BARK 10 [hp_X]/1 mL; TARAXACUM OFFICINALE 10 [hp_X]/1 mL; MILK THISTLE 10 [hp_X]/1 mL; CYNARA SCOLYMUS LEAF 6 [hp_X]/1 mL; SOLIDAGO VIRGAUREA FLOWERING TOP 6 [hp_X]/1 mL
INACTIVE INGREDIENTS: ALCOHOL; WATER

Detox 2559L

INDICATIONS & USAGE SECTION

Formulated for symptoms associated with toxicity such as fatigue, headaches and sluggish elimination.

DOSAGE & ADMINISTRATION SECTION

Directions: Ages 12 and up, take 6 drops by mouth (ages 0 to 11, give 3 drops) at bedtime or as directed by a health professional. Sensitive persons begin with 1 drop and gradually increase to full dose.

OTC - ACTIVE INGREDIENT SECTION

Equal parts of Cynara 6x, Solidago 6x, Taraxacum 6x, Benzoicum acidum 10x, Berber. vulg. 10x, Bryonia 10x, Cantharis 10x, Carduus benedictus 10x, Carduus mar. 10x, Ceanothus 10x, Chelidonium majus 10x, Chionanthus virginica 10x, Cinchona 10x, Dioscorea 10x, Dolichos 10x, Iris versicolor 10x, Juniperus com. 10x, Ptelea 10x, Taraxacum 10x, Nux vom. 15x, Uricum ac 15x.

OTC - PURPOSE SECTION

Formulated for symptoms associated with toxicity such as fatigue, headaches and sluggish elimination.

INACTIVE INGREDIENT SECTION

Inactive Ingredients: USP Purified Water; USP Gluten-free, non-GMO, organic cane alcohol 20%

WARNINGS SECTION

WARNINGS: Keep out of reach of children. Do not use if tamper-evident seal is broken or missing. If symptoms worsen or persist for more than a few days, consult a doctor. If pregnant or breast-feeding, ask a doctor before use.

QUESTIONS SECTION

newtonlabs.net – Questions? 800.448.7256

Newton Laboratories, Inc. FDA Est # 1051203 - Conyers, GA 30013

OTC - PREGNANCY OR BREAST FEEDING SECTION

If pregnant or breast-feeding, ask a doctor before use.

OTC - KEEP OUT OF REACH OF CHILDREN SECTION

Keep out of reach of children.